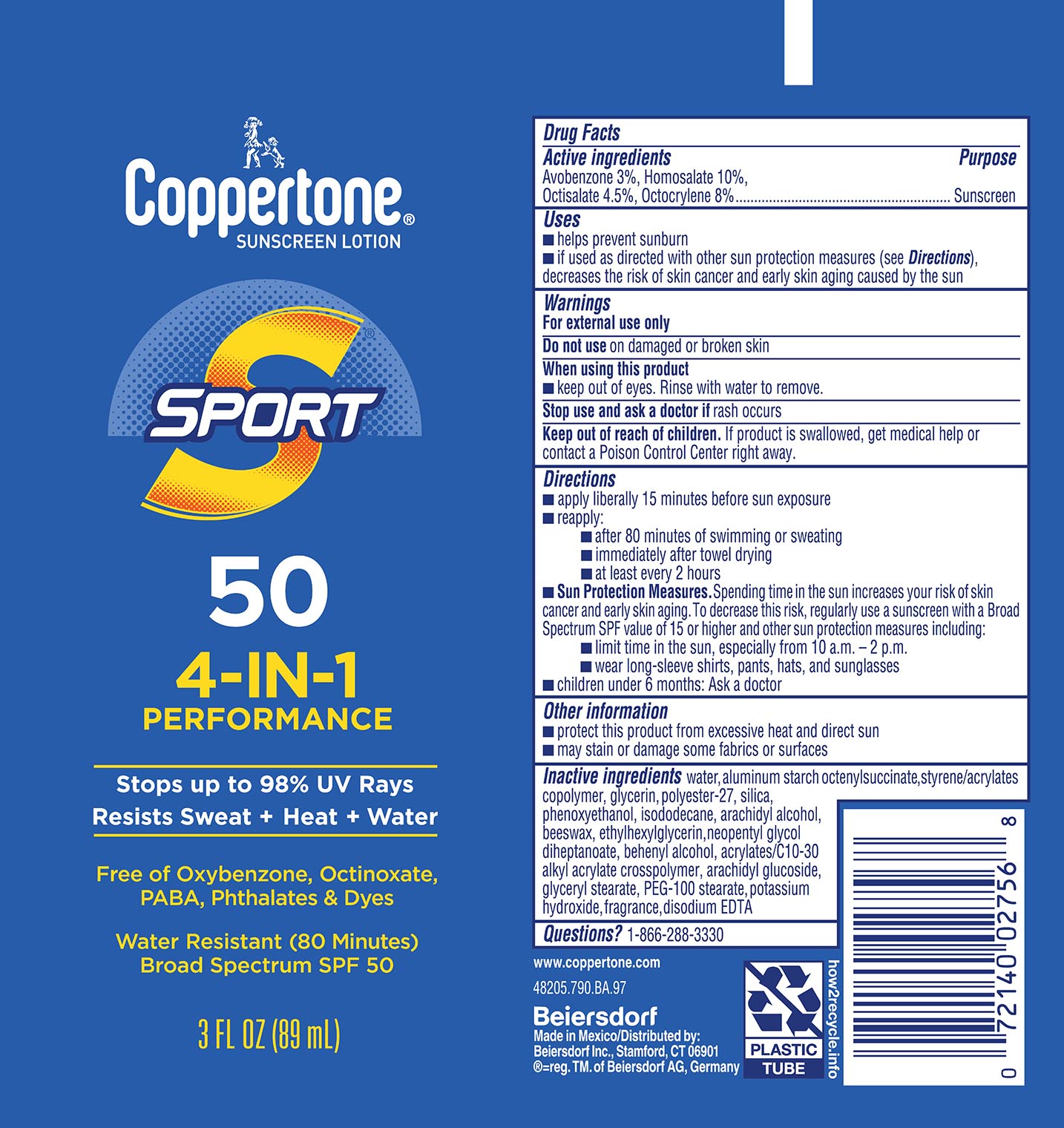 DRUG LABEL: Coppertone Sunscreen SPF 50
NDC: 66800-4107 | Form: LOTION
Manufacturer: Beiersdorf Inc
Category: otc | Type: HUMAN OTC DRUG LABEL
Date: 20251231

ACTIVE INGREDIENTS: OCTISALATE 4.5 g/100 g; OCTOCRYLENE 8 g/100 g; AVOBENZONE 3 g/100 g; HOMOSALATE 10 g/100 g
INACTIVE INGREDIENTS: SILICON DIOXIDE; DISODIUM EDTA-COPPER; PEG-20 STEARATE; STYRENE/ACRYLAMIDE COPOLYMER (MW 500000); ARACHIDYL ALCOHOL; ALUMINUM STARCH OCTENYLSUCCINATE; NEOPENTYL GLYCOL DIHEPTANOATE; DOCOSANOL; ARACHIDYL GLUCOSIDE; ETHYLHEXYLGLYCERIN; GLYCERYL STEARATE SE; GLYCERIN; SYNTHETIC BEESWAX; PHENOXYETHANOL; POTASSIUM HYDROXIDE; CARBOMER INTERPOLYMER TYPE A (55000 CPS); WATER; FRAGRANCE FLORAL ORC0902236; POLYESTER-7; ISODODECANE

Sport Lotion SPF 50

Active ingredients

Avobenzone 3%, Homosalate 10%, Octisalate 4.5%, Octocrylene 8%

Purpose

Sunscreen

Use

■ helps prevent sunburn

Warnings

For external use only

Do not useon damaged or broken skin

Stop use and ask a doctor ifrash occurs

WHEN USING

When using this productkeep out of eyes. Rinse with water to remove.

Keep out of reach of children.If product is swallowed, get medical help or contact a Poison Control Center right away.

Directions

■ apply liberally 15 minutes before sun exposure

■ reapply:

■ after 80 minutes of swimming or sweating

■ immediately after towel drying

■ at least every 2 hours

■ Sun Protection Measures.Spending time in the sun increases your risk of skin cancer and early skin aging. To decrease this risk, regularly use a sunscreen with a Broad Spectrum SPF value of 15 or higher and other sun protection measures including:

■ limit time in the sun, especially from 10 a.m. – 2 p.m.

■ wear long-sleeve shirts, pants, hats, and sunglasses

■ children under 6 months: Ask a doctor

Other information

■ protect this product from excessive heat and direct sun

■ may stain or damage some fabrics or surfaces

Inactive ingredients

water, aluminum starch octenylsuccinate, styrene/acrylates copolymer, glycerin, polyester-27, silica, phenoxyethanol,

isododecane, arachidyl alcohol, beeswax, ethylhexylglycerin, neopentyl glycol

diheptanoate, behenyl alcohol, acrylates/C10-30 alkyl acrylate

crosspolymer, arachidyl glucoside, glyceryl stearate, PEG-100 stearate, potassium

hydroxide, fragrance, disodium EDTA

Questions?

1-866-288-3330

PACKAGE LABEL

Coppertone®Suncreen Lotion

Sport 50

4-IN-1 Performance

Stops up to 98% UV Rays

+Resists

Sweat+Heat+Water

Free of Oxybenzone, Octinoxate, PABA, Phthalates & Dyes

Water Resistant (80 Minutes)

Broad Spectrum SPF 50